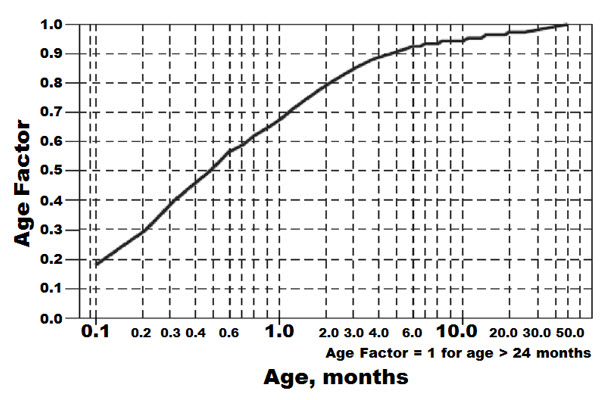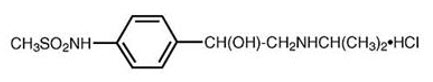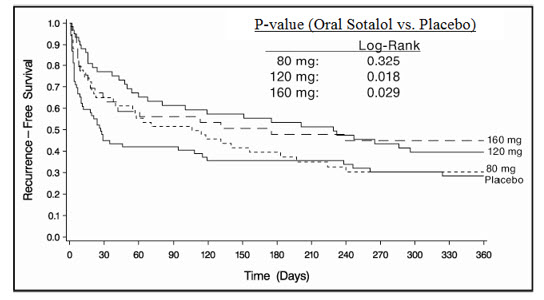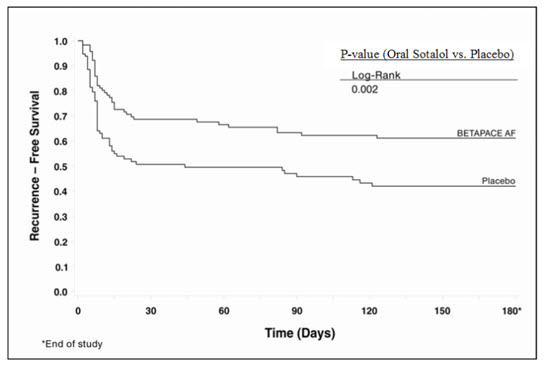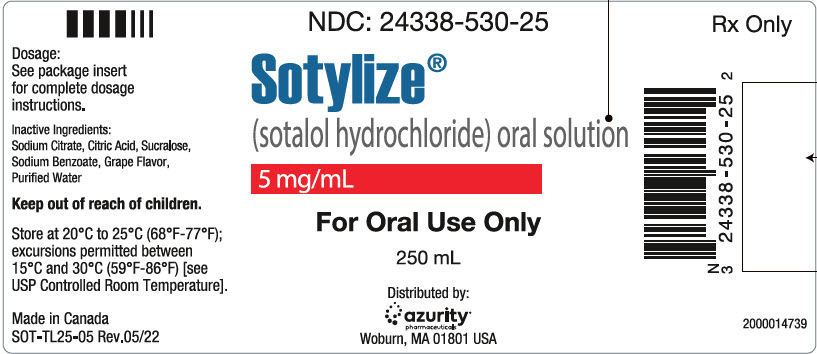 DRUG LABEL: SOTYLIZE
NDC: 24338-530 | Form: SOLUTION
Manufacturer: Azurity Pharmaceuticals, Inc.
Category: prescription | Type: HUMAN PRESCRIPTION DRUG LABEL
Date: 20240124

ACTIVE INGREDIENTS: SOTALOL HYDROCHLORIDE 5 mg/1 mL
INACTIVE INGREDIENTS: SODIUM CITRATE, UNSPECIFIED FORM; CITRIC ACID MONOHYDRATE; SUCRALOSE; SODIUM BENZOATE; WATER

HIGHLIGHTS OF PRESCRIBING INFORMATION

These highlights do not include all the information needed to use SOTYLIZE® safely and effectively. See full prescribing information for SOTYLIZE.
SOTYLIZE (sotalol hydrochloride) oral solution
Initial U.S. Approval: 1992

WARNING: LIFE-THREATENING PROARRHYTHMIA

See full prescribing information for complete boxed warning.

- Sotalol can cause life-threatening ventricular tachycardia associated with QT interval prolongation.
- If the QT interval prolongs to 500 msec or greater, reduce the dose, lengthen the dosing interval, or discontinue the drug.
- Initiate or reinitiate in a facility that can provide cardiac resuscitation and continuous electrocardiographic monitoring.
- Adjust the dosing interval based on creatinine clearance.

1 INDICATIONS AND USAGE

SOTYLIZE is an antiarrhythmic indicated for:

- The treatment of life-threatening ventricular arrhythmias (1.1)
- The maintenance of normal sinus rhythm in patients with highly symptomatic atrial fibrillation/flutter (AFIB/AFL) (1.2)

Limitations of Use

- SOTYLIZE has not been shown to enhance survival in patients with life threatening ventricular arrhythmias (1.1)
- Avoid use in patients with minimally symptomatic or easily reversible AFIB/AFL (1.2)

2 DOSAGE AND ADMINISTRATION

- Initiate therapy at 80 mg twice daily. Increase the dose as needed in increments of 80 mg/day, every 3 days to a maximum 320 mg total daily dose (2.2)
- If creatinine clearance is between 60 and 40 mL/min, administer once daily, if less than 40 mL/min, sotalol is not recommended (2.1)
- Pediatrics: Dosage depends on age (2.4)

3 DOSAGE FORMS AND STRENGTHS

- 5 mg/mL oral solution (3)

4 CONTRAINDICATIONS

For the treatment of AFIB/AFL or ventricular arrhythmias

- Baseline QT interval ˃450 msec (4)
- Sinus bradycardia, 2nd or 3rd degree AV block, sick sinus syndrome (4)
- Congenital or acquired long QT syndromes (4)
- Serum potassium ˂4 mEq/L (4)
- Cardiogenic shock, decompensated heart failure (4)
- Bronchial asthma or related bronchospastic conditions (4)
- Hypersensitivity to sotalol (4)

5 WARNINGS AND PRECAUTIONS

- QT prolongation, bradycardia, AV block, hypotension, worsening heart failure: Reduce dose as needed (5.1)
- Acute exacerbation of coronary artery disease upon cessation of therapy: Do not abruptly discontinue (5.5)
- Correct any electrolyte disturbances (5.5)
- May mask symptoms of hypoglycemia and alter glucose levels; monitor (5.7)

6 ADVERSE REACTIONS

Most common adverse reactions (≥2%) for SOTYLIZE are: fatigue 4%, bradycardia (less than 50 bpm) 3%, dyspnea 3%, proarrhythmia 3%, asthenia 2%, and dizziness 2%.(6)

To report SUSPECTED ADVERSE REACTIONS, contact Azurity Pharmaceuticals, Inc. at 1-800-461-7449 or FDA at 1-800-FDA-1088 or www.fda.gov/medwatch.

7 DRUG INTERACTIONS

- Class I or III Antiarrhythmics or other drugs that prolong the QT interval: Avoid concomitant use (7.1)
- Digoxin, calcium channel blocker: increased risk of bradycardia, hypotension, heart failure (7.2)
- Dosage of insulin or antidiabetic drugs may need adjustment (7.4)
- Aluminum or magnesium-based antacids reduce sotalol exposure (7.7)

8 USE IN SPECIFIC POPULATIONS

- Lactation: Do not breastfeed (8.2)

FULL PRESCRIBING INFORMATION

WARNING: LIFE-THREATENING PROARRHYTHMIA

To minimize the risk of drug-induced arrhythmia, initiate or re-initiate oral sotalol in a facility that can provide cardiac resuscitation and continuous electrocardiographic monitoring.

Sotalol can cause life-threatening ventricular tachycardia associated with QT interval prolongation.

If the QT interval prolongs to 500 msec or greater, reduce the dose, lengthen the dosing interval, or discontinue the drug.

Calculate creatinine clearance to determine appropriate dosing [see Dosage and Administration (2.5)].

1 INDICATIONS AND USAGE

1.1 Life-Threatening Ventricular Arrhythmia

SOTYLIZE is indicated for the treatment of documented, life-threatening ventricular arrhythmias, such as sustained ventricular tachycardia.

Limitation of Use

SOTYLIZE has not been shown to enhance survival in patients with life-threatening ventricular arrhythmias.

1.2 Delay in Recurrence of Atrial Fibrillation/Atrial Flutter (AFIB/AFL)

SOTYLIZE is indicated for the maintenance of normal sinus rhythm [delay in time to recurrence of atrial fibrillation/atrial flutter (AFIB/AFL)] in patients with highly symptomatic AFIB/AFL who are currently in sinus rhythm.

Limitation of Use

Because sotalol can cause life-threatening ventricular arrhythmias, reserve its use for patients in whom AFIB/AFL is highly symptomatic. Patients with paroxysmal AFIB that is easily reversed (by Valsalva maneuver, for example) should usually not be given SOTYLIZE.

2 DOSAGE AND ADMINISTRATION

2.1 General Safety Measures of Oral Sotalol Therapy

Withdraw other antiarrhythmic therapy before starting SOTYLIZE and monitor for a minimum of 2 to 3 plasma half-lives prior to initiating SOTYLIZE therapy if the patient's clinical condition permits [see Drug Interactions (7)].

Hospitalize patients being initiated or re-initiated on sotalol for at least 3 days or until steady-state drug levels are achieved in a facility that can provide cardiac resuscitation and continuous electrocardiographic monitoring. Initiate oral sotalol therapy in the presence of personnel trained in the management of serious arrhythmias. Perform a baseline ECG to determine the QT interval and measure and normalize serum potassium and magnesium levels before initiating therapy. Measure serum creatinine and calculate an estimated creatinine clearance in order to establish the appropriate dosing interval. Monitor QTc 2 to 4 hours after each uptitration in dose.

Discharge patients on sotalol therapy from an in-patient setting with an adequate supply of sotalol to allow uninterrupted therapy until the patient can fill a sotalol prescription.

Advise patients who miss a dose to take the next dose at the usual time. Do not double the dose or shorten the dosing interval.

2.2 Adult Dose for Ventricular Arrhythmia

The recommended initial dose is 80 mg twice daily. This dose may be increased in increments of 80 mg per day every 3 days provided the QTc <500 msec [see Warning and Precautions (5.1)]. Continually monitor patients until steady state blood levels are achieved. In most patients, a therapeutic response is obtained at a total daily dose of 160 to 320 mg/day, given in two or three divided doses. Oral doses as high as 480 to 640 mg once or twice a day have been utilized in patients with refractory life-threatening arrhythmias.

2.3 Adult Dose for Prevention of Recurrence of AFIB/AFL

The recommended initial dose is 80 mg twice daily. This dose may be increased in increments of 80 mg per day every 3 days provided the QTc ˂500 msec [see Warnings and Precautions (5.1)]. Continually monitor patients until steady state blood levels are achieved. Most patients will have a satisfactory response with 120 mg twice daily. Initiation of sotalol in patients with QTc ˃450 msec is contraindicated [see Contraindication (4)].

2.4 Pediatric Dose for Ventricular Arrhythmias or AFIB/AFL

Use the same precautionary measures for children as you would use for adults when initiating and re-initiating sotalol treatment.

For Children Aged About 2 Years and Older

For children aged about 2 years and older with normal renal function, doses normalized for body surface area are appropriate for both initial and incremental dosing. Since the Class III potency in children is not very different from that in adults, reaching plasma concentrations that occur within the adult dose range is an appropriate guide [see Clinical Pharmacology (12.1, 12.3)].

For initiation of treatment, 1.2 mg/kg three times a day (3.6 mg/kg total daily dose) is approximately equivalent to the initial 160 mg total daily dose for adults. Subsequent titration to a maximum of 2.4 mg/kg three times a day (approximately equivalent to the 360 mg total daily dose for adults) can then occur. Titration should be guided by clinical response, heart rate, and QTc, with increased dosing being preferably conducted in-hospital. Allow at least 36 hours between dose increments to attain steady-state plasma concentrations of sotalol in patients with age-adjusted normal renal function.

For Children Aged About 2 Years or Younger

For children aged 2 years or younger, the pediatric dosage should be reduced by a factor that depends upon age, as shown in the following graph (age plotted on a logarithmic scale in months):

For a child aged 1 month, multiply the starting dose by 0.7; the initial starting dose would be (1.2 mg/kg × 0.7)=0.8 mg/kg, administered three times daily. For a child aged about 1 week, multiply the initial starting dose by 0.3; the starting dose would be (1.2 mg/kg × 0.3)=0.4 mg/kg. Use similar calculations for dose titration.

2.5 Dosage for Patients with Renal Impairment

Adults

In any age group with decreased renal function, sotalol doses should be lowered or the intervals between doses increased. It will take much longer to reach steady-state with any dose and/or frequency of administration. Closely monitor heart rate and QTc.

Dose escalations in renal impairment should be done after administration of at least 5 doses at appropriate intervals (Table 1). Sotalol is partly removed by dialysis; specific advice is unavailable on dosing patients on dialysis.

Administer the initial dose of 80 mg and subsequent doses at the intervals listed in Table 1.

Table 1: Dosing Intervals in Renal Impairment
Creatinine Clearance mL/min | Dosing Interval (hours)
>60 | 12
30-59 | 24
10-29 | 36-48
<10 | Dose should be individualized

3 DOSAGE FORMS AND STRENGTHS

Oral solution: 5 mg/mL, in 250 mL or 480 mL bottles.

4 CONTRAINDICATIONS

For the treatment of AFIB/AFL or ventricular arrhythmias, SOTYLIZE is contraindicated in patients with:

- Baseline QT interval ˃450 msec
- Sinus bradycardia, sick sinus syndrome, second and third degree AV block, unless a functioning pacemaker is present
- Congenital or acquired long QT syndromes
- Cardiogenic shock or decompensated heart failure
- Serum potassium <4 mEq/L
- Bronchial asthma or related bronchospastic conditions
- Hypersensitivity to sotalol

5 WARNINGS AND PRECAUTIONS

5.1 QT Prolongation and Proarrhythmia

SOTYLIZE can cause serious and potentially fatal ventricular arrhythmias such as sustained VT/VF, primarily Torsade de Pointes (TdP) type ventricular tachycardia, a polymorphic ventricular tachycardia associated with QT interval prolongation. Factors such as reduced creatinine clearance, female sex, higher doses, reduced heart rate, and history of sustained VT/VF or heart failure increases the risk of TdP. The risk of TdP can be reduced by adjustment of the sotalol dose according to creatinine clearance and by monitoring the ECG for excessive increases in the QT interval [see Dosage and Administration (2.1)].

Correct hypokalemia or hypomagnesemia prior to initiating SOTYLIZE, as these conditions can exaggerate the degree of QT prolongation, and increase the potential for Torsade de Pointes. Special attention should be given to electrolyte and acid-base balance in patients experiencing severe or prolonged diarrhea or patients receiving concomitant diuretic drugs.

Proarrhythmic events must be anticipated not only on initiating therapy, but with every upward dose adjustment [see Dosage and Administration (2.1)].

Avoid use with other drugs known to cause QT prolongation [see Drug Interactions (7.1)].

5.2 Bradycardia/Heart Block/Sick Sinus Syndrome

Sinus bradycardia (heart rate less than 50 bpm) occurred in 13% of patients receiving sotalol in clinical trials, and led to discontinuation in about 3% of patients. Bradycardia itself increases the risk of Torsade de Pointes. Sinus pause, sinus arrest and sinus node dysfunction occur in less than 1% of patients. The incidence of 2nd- or 3rd-degree AV block is approximately 1%.

SOTYLIZE is contraindicated in patients with sick sinus syndrome because it may cause sinus bradycardia, sinus pauses or sinus arrest.

5.3 Hypotension

Sotalol produces significant reductions in both systolic and diastolic blood pressures and may result in hypotension. Monitor hemodynamics in patients with marginal cardiac compensation.

5.4 Heart Failure

New onset or worsening heart failure may occur during initiation or uptitration of sotalol because of its beta-blocking effects. Monitor for signs and symptoms of heart failure and discontinue treatment if symptoms occur.

5.5 Cardiac Ischemia after Abrupt Discontinuation

Following abrupt cessation of therapy with beta-adrenergic blockers, exacerbations of angina pectoris and myocardial infarction may occur. When discontinuing chronically administered SOTYLIZE, particularly in patients with ischemic heart disease, gradually reduce the dosage over a period of 1 to 2 weeks, if possible, and monitor the patient. If angina markedly worsens or acute coronary ischemia develops, treat appropriately and consider use of an alternative beta-blocker. Warn patients not to interrupt therapy without their physician's advice. Because coronary artery disease is common, but may be unrecognized, the abrupt discontinuation of sotalol may unmask latent coronary insufficiency.

5.6 Bronchospasm

Patients with bronchospastic diseases (for example chronic bronchitis and emphysema) should not receive beta-blockers. If SOTYLIZE is to be administered, use the smallest effective dose, to minimize inhibition of bronchodilation produced by endogenous or exogenous catecholamine stimulation of beta-2-receptors.

5.7 Diabetes

Beta-blockers may prevent early warning signs of hypoglycemia, such as tachycardia, and increase the risk for severe or prolonged hypoglycemia at any time during treatment, especially in patients with diabetes mellitus or children and patients who are fasting (i.e., surgery, not eating regularly, or are vomiting). Monitor blood sugar, as appropriate.

5.8 Thyroid Abnormalities

Avoid abrupt withdrawal of beta-blockers in patients with thyroid disease because it may lead to an exacerbation of symptoms of hyperthyroidism, including thyroid storm. Beta-blockers may mask certain clinical signs (for example, tachycardia) of hyperthyroidism.

5.9 Anaphylaxis

While taking beta-blockers, patients with a history of anaphylactic reaction to a variety of allergens may have a more severe reaction on repeated challenge, either accidental, diagnostic, or therapeutic. Such patients may be unresponsive to the usual doses of epinephrine used to treat the allergic reaction.

5.10 Major Surgery

Chronically administered beta-blocking therapy should not be routinely withdrawn prior to major surgery; however, the impaired ability of the heart to respond to reflex adrenergic stimuli may augment the risks of general anesthesia and surgical procedures.

6 ADVERSE REACTIONS

6.1 Clinical Trials Experience

Because clinical trials are conducted under widely varying conditions, adverse reaction rates observed in the clinical trials of a drug cannot be directly compared to rates in the clinical trials of another drug and may not reflect the rates observed in practice.

Adverse reactions that are clearly related to sotalol are those which are typical of its Class II (beta-blocking) and Class III (cardiac action potential duration prolongation) effects and are dose related.

Ventricular Arrhythmias

Serious Adverse Reactions

SOTYLIZE can cause serious and potentially fatal ventricular arrhythmias such as sustained VT/VF, primarily Torsade de Pointes (TdP). [see Warnings and Precautions (5.1)]. The effect on QT and the risk of Torsade de Pointes are both dose related.

Pediatric Patients

In an unblinded multicenter trial of 25 pediatric patients aged ≤ 1 month to 12 years with SVT and/or VT receiving daily doses of 30, 90, and 210 mg/m^2 with dosing every 8 hours for a total of 9 doses, no Torsade de Pointes or other serious new arrhythmias were observed. The clinical trial safety profile in pediatric patients was similar to that in adult patients. Both the Class III and beta-blocking effects of sotalol were linearly related to the plasma concentration [see Clinical Pharmacology (12.2)].

Atrial Fibrillation/Atrial Flutter

Placebo-controlled Clinical Trials

In a pooled clinical trial population consisting of 4 placebo-controlled studies with 275 patients with atrial fibrillation (AFIB/atrial flutter (AFL) treated with 160 to 320 mg of oral sotalol, the following adverse events presented in Table 2 occurred in at least 2% of placebo-treated patients and at a lesser rate than oral sotalol-treated patients. The data are presented by incidence reactions in the oral sotalol and placebo groups by body system and daily dose.

Table 2: Incidence (%) of Common Adverse Reactions (≥2% in the Placebo Group and Less Frequent Than in the Sotalol Groups) in Four Placebo-controlled Studies of Patients with AFIB/AFL
 | Placebo | Oral Sotalol Total Daily Dose
Adverse Reaction | N=282 (%) | 160-240 N=153 (%) | >240-320 N=122 (%)
Bradycardia | 3 | 13 | 12
Diarrhea | 2 | 5 | 6
Nausea/Vomiting | 5 | 8 | 6
Fatigue | 9 | 20 | 19
Hyperhidrosis | 3 | 5 | 5
Weakness | 3 | 5 | 5
Dizziness | 12 | 16 | 13
Headache | 5 | 3 | 12
Dyspnea | 7 | 9 | 10

Overall, discontinuation because of unacceptable adverse events was necessary in 17% of the patients and occurred in 10% of patients less than two weeks after starting treatment. The most common adverse reactions leading to discontinuation of oral sotalol were: fatigue 4.6%, bradycardia 2.4%, proarrhythmia 2.2%, dyspnea 2%, and QT interval prolongation 1.4%.

6.2 Postmarketing Experience

The following adverse reactions have been identified during post-approval use of sotalol. Because these reactions are reported voluntarily from a population of uncertain size, it is not always possible to estimate reliably their frequency or establish a causal relationship to drug exposure:

emotional liability, slightly clouded sensorium, incoordination, vertigo, paralysis, thrombocytopenia, eosinophilia, leukopenia, photosensitivity reaction, fever, pulmonary edema, hyperlipidemia, myalgia, pruritus, alopecia.

7 DRUG INTERACTIONS

7.1 Antiarrhythmics and Other QT Prolonging Drugs

Discontinue Class I or Class III antiarrhythmic agents for at least three half-lives prior to dosing with sotalol. Class Ia antiarrhythmic drugs such as disopyramide, quinidine and procainamide and other Class III drugs (for example, amiodarone) are not recommended as concomitant therapy with sotalol because of their potential to prolong refractoriness [see Warnings and Precautions (5.1)].

7.2 Negative Chronotropes

Digitalis glycosides, diltiazem, verapamil, and beta-blockers slow atrioventricular conduction and decrease heart rate. Concomitant use with negative chronotropes can increase the risk of bradycardia or hypotension.

7.3 Catecholamine-Depleting Agents

Concomitant use of catecholamine-depleting drugs, such as reserpine and guanethidine, with a beta-blocker may produce an excessive reduction of resting sympathetic nervous tone. Monitor such patients for hypotension and/or marked bradycardia which may produce syncope.

7.4 Insulin and Oral Antidiabetics

Hyperglycemia may occur, and the dosage of insulin or antidiabetic drugs may require adjustment [see Warnings and Precautions 5.7]

7.5 Beta-2-Receptor Stimulants

Beta-agonists such as albuterol, terbutaline and isoproterenol may have to be administered in increased dosages when used concomitantly with sotalol.

7.6 Clonidine

Concomitant use with sotalol increases the risk of bradycardia and AV block. Because beta-blockers may potentiate the rebound hypertension sometimes observed after clonidine discontinuation, withdraw sotalol several days before the gradual withdrawal of clonidine to reduce the risk of rebound hypertension.

7.7 Antacids

Avoid administration of oral sotalol within 2 hours of antacids containing aluminum oxide and magnesium hydroxide.

7.8 Drug/Laboratory Test Interactions

The presence of sotalol in the urine may result in falsely elevated levels of urinary metanephrine when measured by flourimetric or photometric methods.

8 USE IN SPECIFIC POPULATIONS

8.1 Pregnancy

Risk Summary

Both the untreated underlying condition in pregnancy and the use of sotalol in pregnancy cause adverse outcomes to the mother and fetus/neonate (see Clinical Considerations). In animal reproduction studies in rats, early resorptions were increased at 15 times the maximum recommended human dose (MRHD). In rabbits an increase in fetal death was observed at 2 times the MRHD administered as single dose. Sotalol did not reveal any teratogenic potential in rats or rabbits at 15 and 2 times the MRHD respectively (see Data).

All pregnancies have a background risk of birth defect, loss, or other adverse outcomes. The estimated background risk of major birth defects and miscarriage for the indicated population is unknown. In the United States (U.S.) general population, the estimated background risk of major birth defects and miscarriage in clinically recognized pregnancies is 2 to 4% and 15 to 20%, respectively.

Clinical Considerations

The incidence of VT is increased and may be more symptomatic during pregnancy. Most tachycardia episodes are initiated by ectopic beats and the occurrence of arrhythmia episodes may, therefore, increase during pregnancy. Breakthrough arrhythmias may also occur during pregnancy, as therapeutic treatment levels may be difficult to maintain due to the increased volume of distribution and increased drug metabolism inherent in the pregnant state.

Fetal/Neonatal Adverse Reactions

Sotalol has been shown to cross the placenta and is found in amniotic fluid. From published observational studies, the potential fetal adverse effects of sotalol use during pregnancy are growth restriction, transient fetal bradycardia, hyperbilirubinemia, hypoglycemia, uterine contractions, and possible intrauterine death. Sotalol may have a greater effect on QT prolongation in the immature heart than in the adult heart, and therefore, conveys an increased risk of serious fetal arrhythmia and/or possible intrauterine death. Monitor newborns for symptoms and adverse reactions associated with beta-blockers.

Labor or Delivery

Generally, risk of arrhythmias increases during labor and delivery process; therefore, considering the proarrhythmia potential of the drug, patients treated with sotalol should be monitored continuously during labor and delivery.

Data

Animal Data

Reproduction studies in rats and rabbits administered sotalol during organogenesis at 15 times and 2 times the MRHD as mg/m^2, respectively, did not reveal any teratogenic potential associated with sotalol.

In pregnant rats, sotalol doses administered during organogenesis at approximately 15 times the MRHD as mg/m^2, increased the number of early resorptions, while no increase in early resorptions was noted at 2 times the MRHD as mg/m^2.

In reproductive studies in rabbits, a sotalol dose (160 mg/kg/day) at 5 times the MRHD as mg/m^2 produced a slight increase in fetal death, and maternal toxicity. However, one study from published data reported an increase in fetal deaths in rabbits receiving a single dose (50 mg/kg) at 2 times the MRHD as mg/m^2 on gestation day 14.

8.2 Lactation

Risk Summary

Limited available data from published literature report that sotalol is present in human milk. The estimated daily infant dose of sotalol received from breastmilk is 0.8-3.4 mg/kg, estimated at 22 to 25.5% of the maternal weight-adjusted dosage of SOTYLIZE (see Data). The amount of drug in breast milk is similar to the neonatal therapeutic dosage. Therefore, there is potential for bradycardia and other symptoms from beta-blockers such as dry mouth, skin or eyes, diarrhea or constipation in the breastfed infant. There is no information regarding the effects of sotalol on milk production. Because of the potential serious adverse reactions to the breastfed child and high level of sotalol in breast milk, advise women not to breastfeed while on treatment with SOTYLIZE.

Data

Sotalol is present in human milk in high levels. A prospective study evaluated 20 paired samples of breast milk and maternal blood from 5 mothers who elected to breastfeed. Breast milk samples had a mean sotalol concentration of 10.5 g µg/mL (± 1.1 µg/mL; range: 4.8 to 20.2 µg/mL compared to a simultaneous mean maternal plasma concentration of 2.3 µg/mL (± 0.3 µg/mL; range: 0.8 to 5.0 µg/mL). The mean milk plasma ratio was 5:4:1 (range: 2.2 to 8.8.). The estimated daily infant dose was 0.8 -3.4 mg/kg, estimated at 22 to 25.5% of the maternal weight-adjusted dosage of sotalol. This is similar to recommended therapeutic dose in neonates. None of the mothers reported any adverse reactions in the breastfed infant.

8.3 Females and Males of Reproductive Potential

Infertility

Based on the published literature, beta-blockers (including sotalol) may cause erectile dysfunction.

8.4 Pediatric Use

The safety and effectiveness of sotalol in children have not been established. However, the Class III electrophysiologic and beta-blocking effects, the pharmacokinetics, and the relationship between the effects (QTc interval and resting heart rate) and drug concentrations have been evaluated in children aged between 3 days and 12 years old [see Dosage and Administration (2.2) and Clinical Pharmacology (12.2)].

Associated side effects of sotalol use in pediatric patients are those typical of a beta-blocking agent, and lead to discontinuation of the drug in 3 to 6% of patients. As in adults, the Class III antiarrhythmic action of sotalol in pediatric patients is associated with a significant proarrhythmic potential for adverse effects. In pediatric patients, the incidence of proarrhythmic side effects of sotalol varies from 0 to 22%; however, sotalol-induced Torsade de Pointes tachycardias are observed less frequently in the pediatric population.

Proarrhythmic effects of sotalol in pediatric patients included increased ventricular ectopy and exacerbation of bradycardia, the latter predominantly in patients with sinus node dysfunction following surgery for congenital cardiac defects. Bradycardia may require emergency pacemaker implantation. Close in-patient monitoring is recommended for several days.

8.6 Renal Impairment

Sotalol is mainly eliminated via the kidneys. Adjust dosing intervals based on creatinine clearance [see Dosage and Administration (2.5)].

10 OVERDOSAGE

Intentional or accidental overdosage with sotalol has resulted in death.

Symptoms and Treatment of Overdosage:

The most common signs to be expected are bradycardia, congestive heart failure, hypotension, bronchospasm and hypoglycemia. In cases of massive intentional overdosage (2 to16 grams) of sotalol the following clinical findings were seen: hypotension, bradycardia, cardiac asystole, prolongation of QT interval, Torsade de Pointes, ventricular tachycardia, and premature ventricular complexes. If overdosage occurs, therapy with sotalol should be discontinued and the patient observed closely. Because of the lack of protein binding, hemodialysis is useful for reducing sotalol plasma concentrations. Patients should be carefully observed until QT intervals are normalized and the heart rate returns to levels >50 bpm.

The occurrence of hypotension following an overdose may be associated with an initial slow drug elimination phase (half-life of 30 hours) thought to be due to a temporary reduction of renal function caused by the hypotension. In addition, if required, the following therapeutic measures are suggested:

Bradycardia or Cardiac Asystole: Atropine, another anticholinergic drug, a beta-adrenergic agonist or transvenous cardiac pacing.

Heart Block: (second and third degree) transvenous cardiac pacemaker.

Hypotension: (depending on associated factors) epinephrine rather than isoproterenol or norepinephrine may be useful.

Bronchospasm: Aminophylline or aerosol beta-2-receptor stimulant. Higher than normal doses of beta-2-receptor stimulants may be required.

Torsade de Pointes: DC cardioversion, transvenous cardiac pacing, epinephrine, magnesium sulfate.

11 DESCRIPTION

SOTYLIZE is an aqueous solution containing sotalol hydrochloride.

Sotalol hydrochloride is a white, crystalline solid with a molecular weight of 308.8. It is hydrophilic, soluble in water, propylene glycol and ethanol, but is only slightly soluble in chloroform. Chemically, sotalol hydrochloride is d,l-N-[4-[1-hydroxy-2-[(1-methylethyl) amino]ethyl]phenyl]methane-sulfonamide monohydrochloride. The molecular formula is C12H20N2O3S HCl and is represented by the following structural formula:

SOTYLIZE is a grape-flavored aqueous solution. Each mL contains 5 mg sotalol HCl. Inactive ingredients are sodium citrate, citric acid, sucralose, sodium benzoate and purified water.

12 CLINICAL PHARMACOLOGY

12.1 Mechanism of Action

Sotalol has both beta-adrenoreceptor blocking (Vaughan Williams Class II) and cardiac action potential duration prolongation (Vaughan Williams Class III) antiarrhythmic properties. The two isomers of sotalol have similar Class III antiarrhythmic effects, while the l-isomer is responsible for virtually all of the beta-blocking activity. The beta-blocking effect of sotalol is non-cardioselective, half maximal at an oral dose of about 80 mg/day and maximal at doses between 320 and 640 mg/day. Sotalol does not have partial agonist or membrane stabilizing activity. Although significant beta-blocker occurs at oral doses as low as 25 mg, significant Class III effects are seen only at daily doses of 160 mg and above.

In children, a Class III electrophysiological effect can be seen at daily doses of 210 mg/m^2 body surface area (BSA). A reduction of the resting heart rate due to the beta-blocking effect of sotalol is observed at daily doses ≥90 mg/m^2 in children.

12.2 Pharmacodynamics

Cardiac Electrophysiological Effects

Sotalol hydrochloride prolongs the plateau phase of the cardiac action potential in the isolated myocyte, as well as in isolated tissue preparations of ventricular or atrial muscle (Class III activity). In intact animals it slows heart rate, decreases AV nodal conduction and increases the refractory periods of atrial and ventricular muscle and conduction tissue.

In human, the Class II (beta-blockers) electrophysiological effects of sotalol are manifested by increased sinus cycle length (slowed heart rate), decreased AV nodal conduction and increased AV nodal refractoriness. The Class III electrophysiological effects in man include prolongation of the atrial and ventricular monophasic action potentials, and effective refractory period prolongation of atrial muscle, ventricular muscle, and atrio-ventricular accessory pathways (where present) in both the anterograde and retrograde directions. With oral doses of 160 to 640 mg/day, the surface ECG shows dose-related mean increases of 40 to100 msec in QT and 10 to40 msec in QTc [see Warning and Precautions (5.1]). No significant alteration in QRS interval was observed.

In a small study (n=25) of patients with implanted defibrillators treated concurrently with sotalol, the average defibrillatory threshold was 6 joules (range 2 to15 joules) compared to a mean of 16 joules for a non-randomized comparative group primarily receiving amiodarone.

Twenty-five children in an unblinded, multicenter trial with supraventricular (SVT) and/or ventricular (VT) tachyarrhythmias, aged between 3 days and 12 years (mostly neonates and infants), received an ascending titration regimen with daily doses of 30, 90 and 210 mg/m^2 with dosing every 8 hours for a total of 9 doses. During steady-state, the respective average increases above baseline of the QTc interval, in msec (%), were 2, 14, and 29 msec at the 3 dose levels. The respective mean maximum increases above baseline of the QTc interval were 23, 36, and 55 msec at the 3 dose levels. The steady-state percent increases in the RR interval were 3, 9 and 12%. The smallest children (BSA<0.33m^2) showed a tendency for larger Class III effects (∆QTc) and an increased frequency of prolongations of the QTc interval as compared with larger children (BSA≥0.33m^2). The beta-blocking effects also tended to be greater in the smaller children (BSA<0.33m^2). Both the Class III and beta-blocking effects of sotalol were linearly related with the plasma concentrations.

Hemodynamics

In a study of systemic hemodynamic function measured invasively in 12 patients with a mean LV ejection fraction of 37% and ventricular tachycardia (9 sustained and 3 non-sustained), a median dose of 160 mg twice daily of sotalol produced a 28% reduction in heart rate and a 24% decrease in cardiac index at 2 hours post-dosing at steady-state. Concurrently, systemic vascular resistance and stroke volume showed non-significant increases of 25% and 8%, respectively. One patient was discontinued because of worsening congestive heart failure. Pulmonary capillary wedge pressure increased significantly from 6.4 mmHg to 11.8 mmHg in the 11 patients who completed the study. Mean arterial pressure, mean pulmonary artery pressure and stroke work index did not significantly change. Exercise and isoproterenol induced tachycardia are antagonized by sotalol, and total peripheral resistance increases by a small amount.

In hypertensive patients, sotalol produces significant reductions in both systolic and diastolic blood pressures. Although sotalol is usually well-tolerated hemodynamically, deterioration in cardiac performance may occur in patients with marginal cardiac compensation [see Warnings and Precautions (5.3)].

12.3 Pharmacokinetics

The pharmacokinetics of the d- and l-enantiomers of sotalol are essentially identical.

Absorption

In healthy subjects, the oral bioavailability of sotalol is 90 to100%. After oral administration, peak plasma concentrations are reached in 2.5 to 4 hours, and steady-state plasma concentrations are attained within 2 to3 days (that is, after 5-6 doses when administered twice daily). Over the oral dosage range 160 to640 mg/day, sotalol displays dose proportionality with respect to plasma concentrations. When administered with a standard meal, the absorption of sotalol was reduced by approximately 20% compared to administration in fasting state.

Distribution

Sotalol does not bind to plasma proteins. Distribution occurs to a central (plasma) and to a peripheral compartment. Sotalol crosses the blood brain barrier poorly.

Metabolism

Sotalol is not metabolized and is not expected to inhibit or induce any CYP450 enzymes.

Excretion

Excretion of sotalol is predominantly via the kidney in the unchanged form, and therefore, lower doses are necessary in conditions of renal impairment [see Dosage and Administration (2.5)]. The mean elimination half-life of sotalol is 12 hours. Dosing every 12 hours results in trough plasma concentrations which are approximately one-half of those at peak.

Specific Populations

Pediatric: The combined analysis of a single-dose and a multiple-dose study with 59 children, aged between 3 days and 12 years, showed the pharmacokinetics of sotalol to be first order. A daily dose of 30 mg/m^2 of sotalol was administered in the single dose study and daily doses of 30, 90 and 210 mg/m^2 were administered every 8 hours in the multi-dose study. After rapid absorption with peak levels occurring on average between 2-3 hours following administration, sotalol was eliminated with a mean half-life of 9.5 hours. Steady-state was reached after 1 to 2 days. The average peak to trough concentration ratio was 2. Body surface area was the most important covariate and more relevant than age for the pharmacokinetics of sotalol. The smallest children (BSA <0.33 m^2) exhibited a greater drug exposure (+59%) than the larger children who showed a uniform drug concentration profile. The intersubject variation for oral clearance was 22%.

Geriatric: Age does not significantly alter the pharmacokinetics of SOTYLIZE, but impaired renal function in geriatric patients can increase the terminal elimination half-life, resulting in increased drug accumulation.

Renal Impairment: Sotalol is mainly eliminated via the kidneys through glomerular filtration and to a small degree by tubular secretion. There is a direct relationship between renal function, as measured by serum creatinine or creatinine clearance, and the elimination rate of sotalol. The half-life of sotalol is prolonged (up to 69 hours) in anuric patients. Adjust doses or dosing intervals based on creatinine clearance [see Dosage and Administration (2.5)].

Hepatic Impairment: Patients with hepatic impairment show no alteration in clearance of sotalol.

Drug-Drug Interactions

Antacids: Administration of oral sotalol within 2 hours of antacids may result in a reduction in Cmax and AUC of 26% and 20%, respectively, and consequently in a 25% reduction in the bradycardic effect at rest. Administration of the antacid two hours after oral sotalol has no effect on the pharmacokinetics or pharmacodynamics of sotalol.

No pharmacokinetic interactions were observed with hydrochlorothiazide or warfarin.

13 NONCLINICAL TOXICOLOGY

13.1 Carcinogenesis, Mutagenesis, Impairment of Fertility

Calculations of safety margins are for the maximum recommended human dose (MRHD) of 640 mg/day of sotalol, administered for life-threatening ventricular arrhythmias in a 60-kg human.

No evidence of carcinogenic potential was observed in rats during a 24-month study at 137 to275 mg/kg/day (approximately 30 times the maximum recommended human oral dose (MRHD) as mg/kg or 5 times the MRHD as mg/m^2) or in mice, during a 24-month study at 4141 to 7122 mg/kg/day (approximately 450 to 750 times the MRHD as mg/kg or 36 to 63 times the MRHD as mg/m^2).

Sotalol has not been evaluated in any specific assay of mutagenicity or clastogenicity.

13.2 Animal Toxicology and/or Pharmacology

No significant reduction in fertility occurred in rats at oral doses of 1000 mg/kg/day (approximately 94 times the MRHD as mg/kg or 15 times the MRHD as mg/m^2) prior to mating, except for a small reduction in the number of offspring per litter.

14 CLINICAL STUDIES

14.1 Ventricular Arrhythmias

In patients with life-threatening arrhythmias [sustained ventricular tachycardia/fibrillation (VT/VF)], sotalol was studied acutely [by suppression of programmed electrical stimulation (PES) induced VT and by suppression of Holter monitor evidence of sustained VT] and, in acute responders, chronically.

In a double-blind, randomized comparison of sotalol and procainamide in 104 patients given intravenously (total of 2 mg/kg sotalol vs. 19 mg/kg of procainamide over 90 minutes), sotalol suppressed PES induction in 30% of patients vs. 20% for procainamide (p=0.2).

In a randomized clinical trial (Electrophysiologic Study Versus Electrocardiographic Monitoring [ESVEM] Trial) in 486 patients comparing the choice of antiarrhythmic therapy by PES suppression vs. Holter monitor selection (in each case followed by treadmill exercise testing) in patients with a history of sustained VT/VF who were also inducible by PES, the effectiveness acutely and chronically of sotalol hydrochloride was compared with 6 other drugs (procainamide, quinidine, mexiletine, propafenone, imipramine, and pirmenol). The Overall response, limited to first randomized drug, was 39% for sotalol and 30% for the pooled other drugs. Acute response rate for first drug randomized using suppression of PES induction was 36% for sotalol vs. a mean of 13% for the other drugs. Using the Holter monitoring endpoint (complete suppression of sustained VT, 90% suppression of NSVT, 80% suppression of PVC pairs, and at least 70% suppression of PVCs), sotalol yielded 41% response vs. 45% for the other drugs combined. Among responders placed on long-term therapy identified acutely as effective (by either PES or Holter), sotalol, when compared to the pool of other drugs, had the lowest two-year mortality (13% vs. 22%), the lowest two-year VT recurrence rate (30% vs. 60%), and the lowest withdrawal rate (38% vs. about 75 to 80%). The most commonly used doses of orally administered sotalol in this trial were 320 to480 mg/day (66% of patients), with 16% receiving 240 mg/day or less and 18% receiving 640 mg or more.

It cannot be determined, however, in the absence of a controlled comparison of sotalol vs. no pharmacologic treatment (for example, in patients with implanted defibrillators) whether sotalol response causes improved survival or identifies a population with a good prognosis.

Sotalol has not been shown to enhance survival in patients with ventricular arrythmias.

14.2 Supraventricular Arrhythmias

Sotalol has been studied in patients with symptomatic AFIB/AFL in two principal studies, one in patients with primarily paroxysmal AFIB/AFL, the other in patients with primarily chronic AFIB.

In one study, a U.S. multicenter, randomized, placebo-controlled, double-blind, dose-response trial of patients with symptomatic primarily paroxysmal AFIB/AFL, three fixed dose levels of sotalol (80 mg, 120 mg and 160 mg) twice daily and placebo were compared in 253 patients. In patients with reduced creatinine clearance (40 to 60 mL/min) the same doses were given once daily. Patients were excluded for the following reasons: QT >450 msec; creatinine clearance <40 mL/min; intolerance to beta-blockers; bradycardia-tachycardia syndrome in the absence of an implanted pacemaker; AFIB/AFL was asymptomatic or was associated with syncope, embolic CVA or TIA; acute myocardial infarction within the previous 2 months; congestive heart failure; bronchial asthma or other contraindications to beta-blocker therapy; receiving potassium losing diuretics without potassium replacement or without concurrent use of ACE-inhibitors; uncorrected hypokalemia (serum potassium <3.5 mEq/L) or hypomagnesemia (serum magnesium <1.5 mEq/L); received chronic oral amiodarone therapy for >1 month within previous 12 weeks; congenital or acquired long QT syndromes; history of Torsade de Pointes with other antiarrhythmic agents which increase the duration of ventricular repolarization; sinus rate <50 bpm during waking hours; unstable angina pectoris; receiving treatment with other drugs that prolong the QT interval; and AFIB/AFL associated with the Wolff-Parkinson-White (WPW) syndrome. If the QT interval increased to ≥520 msec (or JT ≥430 msec if QRS >100 msec) the drug was discontinued. The patient population in this trial was 64% male, and the mean age was 62 years. No structural heart disease was present in 43% of the patients. Doses were administered once daily in 20% of the patients because of reduced creatinine clearance.

Sotalol was shown to prolong the time to the first symptomatic, ECG-documented recurrence of AFIB/AFL, as well as to reduce the risk of such recurrence at both 6 and 12 months. The 120 mg dose was more effective than 80 mg, but 160 mg did not appear to have an added benefit. Note that these doses were given twice or once daily, depending on renal function. The results are shown in Figure 1, Table 3 and Table 4.

Figure 1: Study 1 – Time to First ECG-Documented Recurrence of Symptomatic AFIB/AFL Since Randomization

Table 3: Study 1 – Patient Status at 12 Months
 | Placebo | Sotalol Dose
 | Placebo | 80 mg | 120 mg | 160 mg
Randomized | 69 | 59 | 63 | 62
On treatment in NSR at 12 months without recurrence [Symptomatic AFIB/AFL] | 23% | 22% | 29% | 23%
Recurrence [Efficacy endpoint of Study 1; study treatment stopped.] | 67% | 58% | 49% | 42%
D/C for AEs | 6% | 12% | 18% | 29%
Note that columns do not add up to 100% due to discontinuations (D/C) for "other" reasons.

Table 4: Study 1 – Median Time to Recurrence of Symptomatic AFIB/AFL and Relative Risk (vs. Placebo) at 12 Months
 | Placebo n=69 | Oral Sotalol Dose
 | Placebo n=69 | 80 mg n=59 | 120 mg n=63 | 160 mg n=62
p-value vs. placebo |  | 0.325 | 0.018 | 0.029
Relative Risk (RR) to placebo |  | 0.81 | 0.59 | 0.59
Median time to recurrence (days) | 27 | 106 | 229 | 175

Discontinuation because of adverse events was dose related.

In a second multicenter, randomized, placebo-controlled, double-blind study of 6 months duration in 232 patients with chronic AFIB, oral sotalol was titrated over a dose range from 80 mg/day to 320 mg/day. The patient population of this trial was 70% male with a mean age of 65 years. Structural heart disease was present in 49% of the patients. All patients had chronic AFIB for >2 weeks but <1 year at entry with a mean duration of 4.1 months. Patients were excluded if they had significant electrolyte imbalance, QTc >460 msec, QRS >140 msec, any degree of AV block or functioning pacemaker, uncompensated cardiac failure, asthma, significant renal disease (estimated creatinine clearance <50 mL/min), heart rate <50 bpm, myocardial infarction or open heart surgery in past 2 months, unstable angina, infective endocarditis, active pericarditis or myocarditis, ≥ 3 DC cardioversions in the past, medications that prolonged QT interval, and previous amiodarone treatment.

After successful cardioversion patients were randomized to receive placebo (n=114) or sotalol (n=118), at a starting dose of 80 mg twice daily. If the initial dose was not tolerated it was decreased to 80 mg once daily, but if it was tolerated it was increased to 160 mg twice daily. During the maintenance period 67% of treated patients received a dose of 160 mg twice daily, and the remainder received doses of 80 mg once daily (17%) and 80 mg twice daily (16%).

Tables 5 and 6 show the results of the trial. There was a longer time to ECG-documented recurrence of AFIB and a reduced risk of recurrence at 6 months compared to placebo.

Table 5: Study 2 – Patient Status at 6 Months
 | Placebo n=114 | Oral Sotalol n=118
On treatment in NSR at 6 months without recurrence [Symptomatic or asymptomatic AFIB/AFL] | 29% | 45%
Recurrence [Efficacy endpoint of Study 2; study treatment stopped.] | 67% | 49%
D/C for AEs | 3% | 6%
Death | 1%

Table 6: Study 2 – Median Time to Recurrence of Symptomatic AFIB/AFL/Death and Relative Risk (vs. Placebo) at 6 Months
 | Placebo | Oral Sotalol | Relative Risk | P-value
Median time to recurrence (days) | 44 | >180 | 0.55 | 0.002

Figure 2: Study 2 – Time to First ECG-Documented Recurrence of Symptomatic AFIB/AFL/Death Since Randomization

16 HOW SUPPLIED/STORAGE AND HANDLING

SOTYLIZE (sotalol hydrochloride) is supplied as follows:

- NDC 24338-530-25, 5 mg/mL: 250 mL bottle
- NDC 24338-530-48, 5 mg/mL: 480 mL bottle

STORAGE AND HANDLING

Store at 20°C to 25°C (68°F -77°F); excursions permitted between 15°C and 30°C (59°F-86°F) [see USP Controlled Room Temperature].

17 PATIENT COUNSELING INFORMATION

- Advise patients to contact their healthcare provider in the event of syncope, pre-syncopal symptoms and cardiac palpitations.
- Advise patients to contact their healthcare provider in the event of conditions conducive to electrolyte changes such as severe diarrhea, unusual sweating, vomiting, less appetite than normal or excessive thirst [see Warnings and Precautions (5.1)].
- Advise patients to not change the SOTYLIZE dose prescribed by their healthcare provider.
- Advise patients that they should not miss a dose, but if they do miss a dose they should not double the next dose to compensate for the missed dose: they should take the next dose at the regularly scheduled time [see Dosage and Administration (2)].
- Advise patients to not interrupt or discontinue SOTYLIZE without their physician's advice, that they should get their prescription for sotalol filled and refilled on-time so they do not interrupt treatment [see Dosage and Administration (2)].
- Inform patients or caregivers that there is a risk of hypoglycemia when SOTYLIZE is given to patients who are fasting or who are vomiting. Inform patients to notify their healthcare provider if they experience symptoms of hypoglycemia. [See Warnings and Precautions (5.7)].
- Advise patients not to start taking other medications without first discussing new medications with their healthcare provider.
- Advise patients to avoid taking SOTYLIZE within 2 hours of taking antacids that contain aluminum oxide or magnesium hydroxide [see Drug Interactions (7.7)].
- Advise patients to contact their healthcare provider if they develop bradycardia.
- Advise patients that if overdose occurs or they take too much SOTYLIZE, take their SOTYLIZE medicine bottle with them and go to the nearest emergency room immediately. Overdoses can potentially cause life-threatening abnormal heart beats and possibly death.

Lactation

- Advise women not to breastfeed while on treatment with SOTYLIZE [see Use in Specific Populations (8.2)]

Rx Only

Manufactured for:
azurity®
pharmaceuticals
Woburn, MA 01801

Manufactured by:
Patheon Inc.
Whitby Region Operations
111 Consumers Drive
Whitby, ON L1N 5Z5 Canada

Patent: https://azurity.com/patents

Distributed by: Azurity Pharmaceuticals, Inc. Woburn, MA 01801

SOTYLIZE® is a registered trademark of Azurity Pharmaceuticals, Inc.

PN: SOT-PI-04

PRINCIPAL DISPLAY PANEL - 250 mL Bottle Label

NDC: 24338-530-25

Sotylize®
(sotalol hydrochloride) oral solution

5 mg/mL

For Oral Use Only

250 mL

Distributed by:
azurity®
pharmaceuticals
Woburn, MA 01801 USA